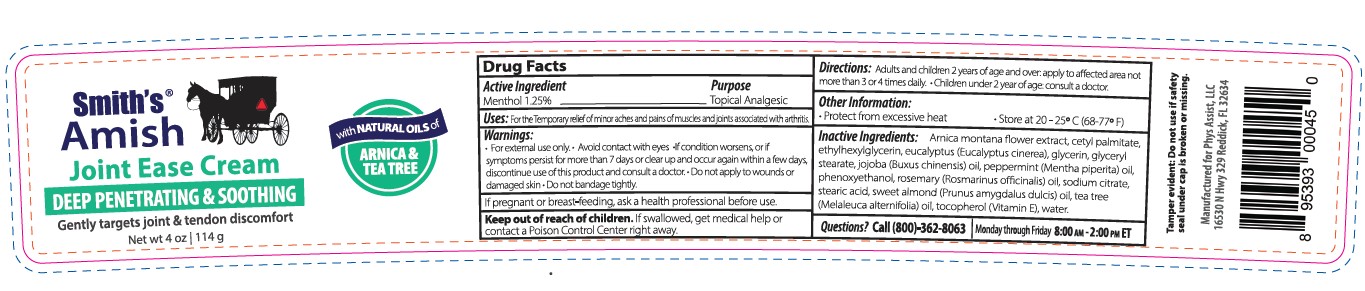 DRUG LABEL: Joint Ease
NDC: 72609-045 | Form: CREAM
Manufacturer: Smith Amish, LLC
Category: otc | Type: HUMAN OTC DRUG LABEL
Date: 20251212

ACTIVE INGREDIENTS: MENTHOL 1.25 g/100 g
INACTIVE INGREDIENTS: ALMOND OIL; JOJOBA OIL; GLYCERYL MONOSTEARATE; PEPPERMINT OIL; .ALPHA.-TOCOPHEROL; ARNICA MONTANA WHOLE; CETYL PALMITATE; SODIUM CITRATE; STEARIC ACID; TEA TREE OIL; WATER; ROSEMARY OIL; EUCALYPTUS OIL; GLYCERIN; PHENOXYETHANOL

Smith Amish Joint Ease Cream (4oz) - 72609-045-04

Drug Facts Active Ingredient

Menthol 1.25%

Purpose

Topical analgesic

Uses

For the termporary relief of minor aches and pains of muscles and joints associated with arthritis.

Warnings

For external use only
Avoid contact with eyes

STOP USE

- If condition worsens, or if symptoms persist for more than 7 days or cler up and occur again within a few days,, discontinue use of this product and consult a doctor. Do not bandage tightly.

PREGNANCY OR BREAST FEEDING

If pregnant or breast-feeding, ask a health professional before use.

Keep out of reach of children.

If swallowed, get medical help or contact a Poison Control Center right away.

Directions

Adults and children 2 years of age and over: apply to affected area not more than 3 to 4 times daily. Children under 2 years of age consult a doctor.

Other information

Protect from excessive heat

Store at 20-25oC (68-77F)

Inactive Ingredients

Arnica montana flower extract, cetyl palmitate, ethylhexylglycerin, eucalyptus (Eucalyptus cinerea), glycerin, glyceryl stearate, jojoba (Buxus chinensis) oil, peppermint (mentha piperita) oil, phenoxyethanol, rosemary (Rosmariunus officinalis) oil, sodium citrate, stearic acid, sweet almond (Prunus amydgalus dulcis) oil, tea tree (Melaleuca alternifolia) oil, tocopherol (Vitamin E), water

Questions?

Call (866) 419-3567

Monday through Friday 8:00am - 2:00pm ET

Tamper evident: Do not use if safety seal under cap is broken or missing.

Manufactured for Smith Amish LLC 16350 N Hwy 329 Reddick, FL 32634

Label

Smith Amish Joint Ease Cream (72609-045-04)

Deep Penetrating & Soothing

Gently targets joint & tendon discomfort

Net wt. 4oz (114g)